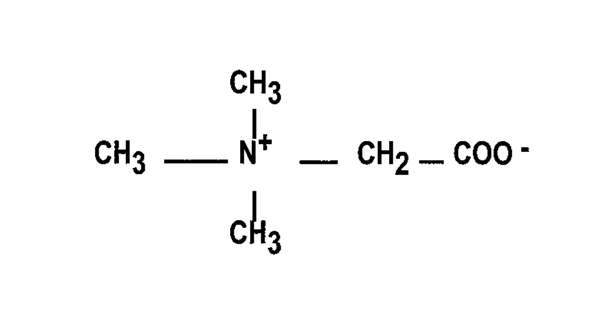 DRUG LABEL: Unknown
Manufacturer: Jazz Pharmaceuticals, Inc.
Category: prescription | Type: Human prescription drug label
Date: 20070331

Cystadane® (betaine anhydrous for oral solution)

Rx only

DESCRIPTION

Cystadane® (betaine anhydrous for oral solution) is an agent for the treatment of homocystinuria. Cystadane is a white, granular, hygroscopic powder. It contains no ingredients other than anhydrous betaine. Betaine anhydrous powder is very soluble in water, soluble in methanol and ethanol, and sparingly soluble in ether.

The chemical name of betaine anhydrous powder is trimethylglycine. It has a molecular weight of 117.15. The structural formula is:

CLINICAL PHARMACOLOGY

When administered in recommended oral dosage to children or adults, Cystadane acts as a methyl group donor in the remethylation of homocysteine to methionine in patients with homocystinuria. As a result, toxic blood levels of homocysteine are reduced in these patients, usually to 20-30 percent or less of pre-treatment levels.

Elevated homocysteine blood levels are associated with clinical problems such as a cardiovascular thrombosis, osteoporosis, skeletal abnormalities, and optic lens dislocation. Plasma levels of homocysteine were decreased in nearly all patients treated with betaine. In observational studies without concurrent controls, clinical improvement was reported by the treating physicians in about three-fourths of patients taking betaine. Many of these patients were also taking other therapies such as vitamin B6 (pyridoxine), vitamin B12 (cobalamin), and folate with variable biochemical responses. In most cases studied, adding betaine resulted in a further reduction of homocysteine.

Betaine was observed to lower plasma homocysteine levels in the three types of homocystinuria, i.e., cystathionine beta-synthase (CBS) deficiency; 5,10-methylenetetrahydrofolate reductase (MTHFR) deficiency; and cobalamin cofactor metabolism (cbl) defect.

Betaine has also been demonstrated to increase low plasma methionine and S-adenosylmethionine (SAM) levels in patients with MTHFR deficiency and cbl defect.

In CBS-deficient patients, large increases in methionine levels over baseline have been observed.

Betaine occurs naturally in the body. It is a metabolite of choline and is present in small amounts in foods such as beets, spinach, cereals, and seafood.

Pharmacokinetic studies of betaine are not available. Plasma levels of betaine have not been measured in patients and have not been correlated to homocysteine levels. However, pharmacodynamic measurements, i.e., monitoring of plasma homocysteine levels, have demonstrated that the onset of action of betaine is within several days and that a steady state in response to dosage is achieved within several weeks. Patients have taken betaine for many years without evidence of tolerance.

INDICATIONS AND USAGE

Cystadane (betaine anhydrous for oral solution) is indicated for the treatment of homocystinuria to decrease elevated homocysteine blood levels. Included within the category of homocystinuria are deficiencies or defects in:

1. cystathionine beta-synthase (CBS),
2. 5,10-methylenetetrahydrofolate reductase (MTHFR),
3. cobalamin cofactor metabolism (cbl).

Patient response to Cystadane can be monitored by homocysteine plasma levels (see DOSAGE AND ADMINISTRATION). Response usually occurs within a week and steady state within a month.

Cystadane has been administered concomitantly with vitamin B6 (pyridoxine), vitamin B12 (cobalamin), and folate.

PRECAUTIONS

General

Therapy with Cystadane should be directed by physicians knowledgeable in the management of patients with homocystinuria.

Hypermethioninemia

Patients with homocystinuria due to cystathionine beta-synthase (CBS) deficiency may also have elevated plasma methionine concentrations. Treatment with Cystadane may further increase methionine concentrations due to the remethylation of homocysteine to methionine. Cerebral edema has been reported in patients with hypermethioninemia, including a few patients treated with Cystadane. Plasma methionine concentrations should be monitored in patients with CBS deficiency. Plasma methionine concentrations should be kept below 1,000 umol/L through dietary modification and, if necessary, a reduction of Cystadane dose.

Information for patients

1. Shake bottle lightly before removing cap.
2. Measure with the scoop provided.
3. One level scoop (1.7 cc) is equivalent to 1 gram of betaine anhydrous powder. Measure the number of scoops your physician has prescribed.
4. Mix with 4 to 6 ounces (120 to 180 mL) of water, juice, milk, or formula until completely dissolved, or mix with food, then ingest immediately.

Always replace the cap tightly after using. Protect from moisture.

Carcinogenesis, mutagenesis, impairment of fertility

Long-term carcinogenicity and fertility studies have not been conducted on betaine. No evidence of genotoxicity was demonstrated in the following tests: Metaphase Analysis of Human Lymphocytes; Bacterial Reverse Mutation Assay; and Mouse Micronucleus Test.

Pregnancy

Pregnancy Category C. Animal reproduction studies have not been conducted with betaine. It is also not known whether betaine can cause fetal harm when administered to a pregnant woman or can affect reproduction capacity. Cystadane (betaine anhydrous for oral solution) should be given to a pregnant woman only if clearly needed.

Nursing mothers

It is not known whether betaine is excreted in human milk (although its metabolic precursor, choline, occurs at high levels in human milk). Because many drugs are excreted in human milk, caution should be exercised when Cystadane is administered to a nursing woman.

Pediatric use

The majority of case studies of homocystinuria patients treated with betaine have been pediatric patients. The disorder, in its most severe form, can be manifested within the first months or years of life by lethargy, failure to thrive, developmental delays, seizures, or optic lens displacement. Patients have been treated successfully without adverse effects within the first months or years of life with dosages of 6 grams per day or more of betaine with resultant biochemical and clinical improvement. However, dosage titration may be preferable in pediatric patients (see DOSAGE AND ADMINISTRATION).

ADVERSE REACTIONS

Adverse reactions to betaine have been minimal. In a survey study of physicians who had treated a total of 111 homocystinuria patients with betaine, the types of adverse effects and the number of patients experiencing them were as follows:

Nausea | 2 | “Caused odor” | 1
GI distress | 2 | Questionable psychological changes | 1
Diarrhea | 1 | “Aspirated the powder” | 1
Unspecified problem | 1

A few cases of cerebral edema have been reported secondary to severe hypermethioninemia in patients with cystathionine beta-synthase (CBS) deficiency treated with Cystadane. See PRECAUTIONS: Hypermethioninemia.

OVERDOSAGE

In an acute toxicology study in rats, death frequently occurred at doses equal to or greater than 10,000 mg/kg.

DOSAGE AND ADMINISTRATION

The usual dosage used in adult and pediatric patients is 6 grams per day administered orally in divided doses of 3 grams two times per day. Dosages of up to 20 grams per day have been necessary to control homocysteine levels in some patients. In pediatric patients less than 3 years of age, dosage may be started at 100 mg/kg/day and then increased weekly by 50 mg/kg increments. In one study by Matthewsi et al., pharmacokinetic and pharmacodynamic simulation indicated minimal benefit from exceeding a twice-daily dosing schedule and a 150 mg/kg/day dosage for betaine. Dosage in all patients can be gradually increased until plasma total homocysteine is undetectable or present only in small amounts. Plasma methionine concentrations should be monitored in patients with CBS-deficiency. See PRECAUTIONS: Hypermethioninemia.

The prescribed amount of Cystadane (betaine anhydrous for oral solution) should be measured with the measuring scoop provided (one level 1.7 cc scoop is equal to 1 gram of betaine anhydrous powder) and then dissolved in 4 to 6 ounces (120 to 180 mL) of water, juice, milk, or formula, or mixed with food for immediate ingestion.

HOW SUPPLIED

Cystadane is available in plastic bottles containing 180 grams of betaine anhydrous. Each bottle is equipped with a plastic child-resistant cap and is supplied with a polystyrene measuring scoop. One level scoop (1.7 cc) is equal to 1 gram of betaine anhydrous powder.

NDC 68727-400-01

180g/bottle

DIN 02238526

Store at room temperature, 15° - 30°C (59° - 86°F).

For questions of a medical nature in the U.S. or Canada, call
1-888-867-7426.

Cystadane® can be ordered by calling Jazz Pharmaceuticals, Inc. Customer Service at 1-800-359-4304 or by contacting your local wholesaler.

Distributed in the U.S. by:

Jazz Pharmaceuticals, Inc.

Palo Alto, CA 94304

Distributed in Canada by:

Jazz Pharmaceuticals, Inc.

Scarborough, Ontario

M1H 2W4

Revision Date: August 2006

Part No. CYS PI-8585

i Matthews A, Johnson TN, Rostami-Hodjegan A, Chakrapani A, et al. An indirect response model of homocysteine suppression by betaine: optimizing the dosage regimen of betaine in homocystinuria. Br J Clin Pharmacol 2002; 54:140-146.